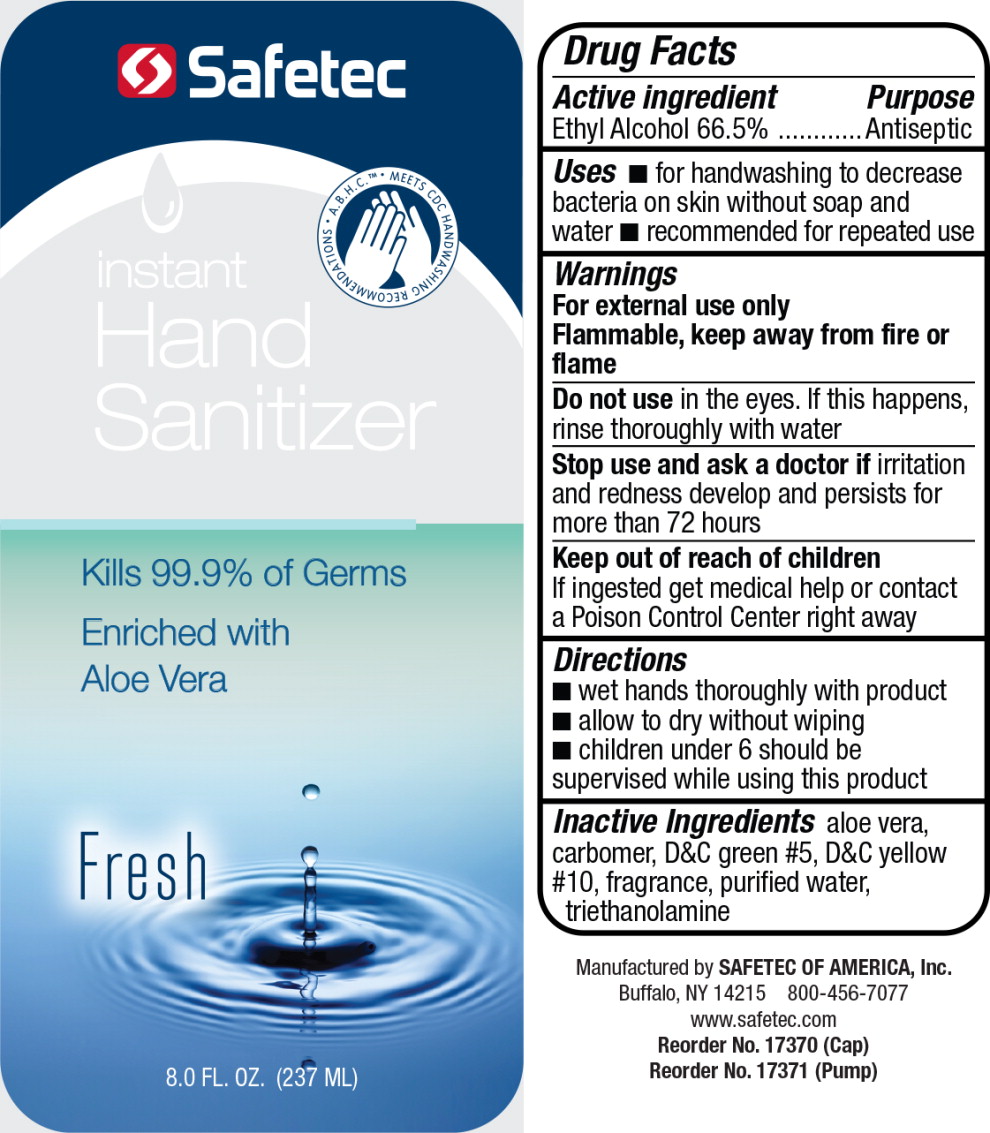 DRUG LABEL: Instant Hand Sanitizer
NDC: 61010-1112 | Form: GEL
Manufacturer: Safetec of America, Inc.
Category: otc | Type: HUMAN OTC DRUG LABEL
Date: 20260116

ACTIVE INGREDIENTS: ALCOHOL 665 mL/1 L
INACTIVE INGREDIENTS: CARBOMER HOMOPOLYMER TYPE C (ALLYL PENTAERYTHRITOL CROSSLINKED); ALOE VERA LEAF; D&C GREEN NO. 5; D&C YELLOW NO. 10; WATER; TROLAMINE

61010-1112, Instant Hand Sanitizer

Drug Facts

Active Ingredients

Ethyl Alcohol 66.5%

Purpose

Antiseptic

Uses

- for handwashing to decrease bacteria on skin without soap and water
- recommended for repeated use

Warnings

For external use only

Flammable, keep away from fire or flame

DO NOT USE

Do not usein the eyes. If this happens, rinse thoroughly with water

Stop use and ask doctor ifirritation and redness develop and persists for more than 72 hours

KEEP OUT OF REACH OF CHILDREN

Keep out of reach of childrenIf ingested get medical help or contact a Poison Control Center right away

Directions

- wet hands & wrists thoroughly with product
- allow to dry without wiping
- children under 6 should be supervised while using this product

Inactive ingredients

aloe vera, carbomer, D&C green #5, D&C yellow#10, fragrance, purified water, triethanolamine

Manufactured by
SAFETEC OF AMERICA, Inc.
Buffalo, NY 14215 800-456-7077
www.safetec.com

PRINCIPAL DISPLAY PANEL – 8 fl. oz. Bottle Label

Safetec

instant

Hand

Sanitizer

Kills 99.9% of Germs

Enriched with

Aloe Vera

Fresh

8.0 FL. OZ. (237 ML)